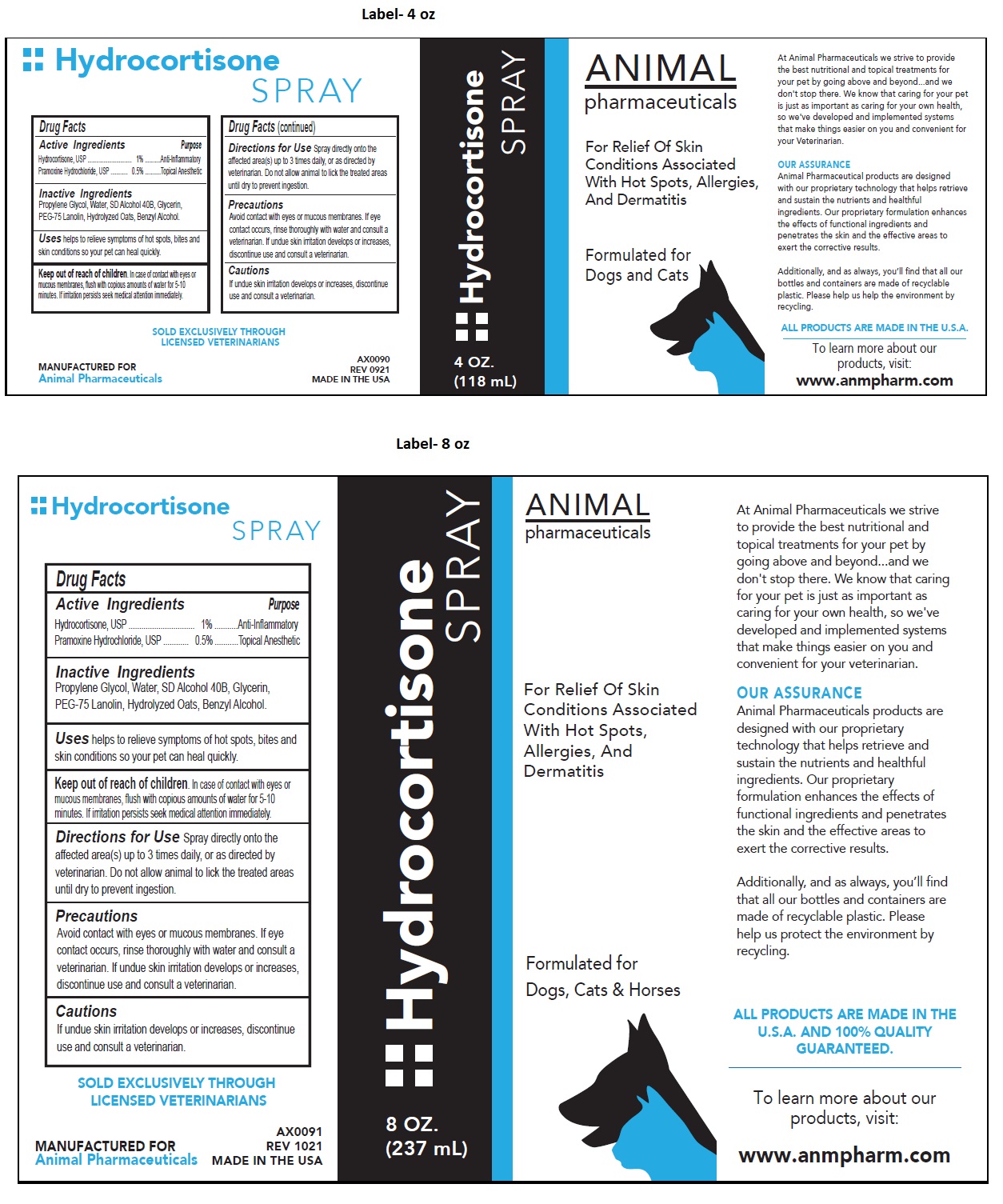 DRUG LABEL: Hydrocortisone
NDC: 68898-127 | Form: SPRAY
Manufacturer: Animal Pharmaceuticals
Category: animal | Type: OTC ANIMAL DRUG LABEL
Date: 20211105

ACTIVE INGREDIENTS: HYDROCORTISONE 1 g/100 mL; PRAMOXINE HYDROCHLORIDE 0.5 g/100 mL
INACTIVE INGREDIENTS: PROPYLENE GLYCOL; WATER; ALCOHOL; GLYCERIN; PEG-75 LANOLIN; OAT; BENZYL ALCOHOL

Hydrocortisone SPRAY

Active Ingredients

Hydrocortisone, USP ............................... 1%
Pramoxine Hydrochloride, USP ............ 0.5%

Purpose

Anti-Inflammatory
Topical Anesthetic

Inactive Ingredients

Propylene Glycol, Water, SD Alcohol 40B, Glycerin, PEG-75 Lanolin, Hydrolyzed Oats, Benzyl Alcohol.

Uses

helps to relieve symptoms of hot spots, bites and skin conditions so your pet can heal quickly.

Keep out of reach of children. In case of contact with eyes or mucous membranes, flush with copious amounts of water for 5-10 minutes. If irritation persists seek medical attention immediately.

Directions for Use

Spray directly onto the affected area(s) up to 3 times daily, or as directed by veterinarian. Do not allow animal to lick the treated areas until dry to prevent ingestion.

Precautions

Avoid contact with eyes or mucous membranes. If eye contact occurs, rinse thoroughly with water and consult a veterinarian. If undue skin irritation develops or increases, discontinue use and consult a veterinarian.

Cautions

If undue skin irritation develops or increases, discontinue use and consult a veterinarian.

For Relief Of Skin Conditions Associated With Hot Spots, Allergies, And Dermatitis

Formulated for Dogs, Cats & Horses

At Animal Pharmaceuticals we strive to provide the best nutritional and topical treatments for your pet by going above and beyond...and we don't stop there. We know that caring for your pet is just as important as caring for your own health, so we've developed and implemented systems that make things easier on you and convenient for your Veterinarian.

OUR ASSURANCE

Animal Pharmaceutical products are designed with our proprietary technology that helps retrieve and sustain the nutrients and healthful ingredients. Our proprietary formulation enhances the effects of functional ingredients and penetrates the skin and the effective areas to exert the corrective results.

Additionally, and as always, you’ll find that all our bottles and containers are made of recyclable plastic. Please help us help the environment by recycling.

ALL PRODUCTS ARE MADE IN THE U.S.A. AND 100% QUALITY GUARANTEED.

To learn more about our products, visit:
www.anmpharm.com

SOLD EXCLUSIVELY THROUGH LICENSED VETERINARIANS

MANUFACTURED FOR
Animal Pharmaceuticals

AX0090
REV 0921
AX0091
REV 1021

MADE IN THE USA